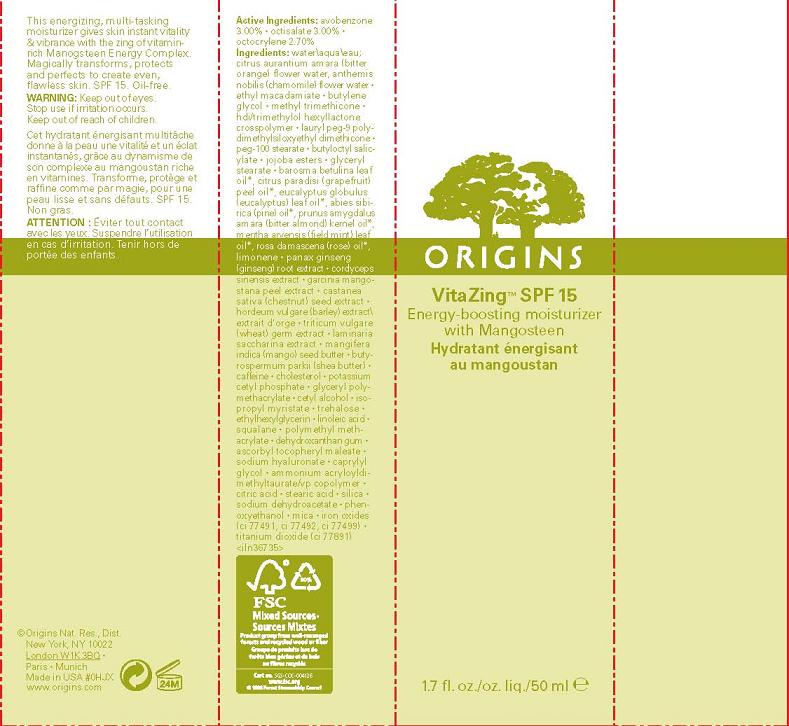 DRUG LABEL: VITAZING
NDC: 59427-705 | Form: CREAM
Manufacturer: ORIGINS NATURAL RESOURCES INC
Category: otc | Type: HUMAN OTC DRUG LABEL
Date: 20110114

ACTIVE INGREDIENTS: AVOBENZONE 3.0 mL/100 mL; OCTISALATE 3.0 mL/100 mL; OCTOCRYLENE 2.7 mL/100 mL
INACTIVE INGREDIENTS: WATER; BUTYLENE GLYCOL

ACTIVE INGREDIENT

active ingredients: avobenzone 3.00% [] octisalate 3.00% [] octocrylene 2.70%

INACTIVE INGREDIENT

inactive ingredients: water\aqua\eau; citrus aurantium amara (bitter orange) flower water, anthemis nobilis (chamomile) flower extract [] ethyl macadamiate [] butylene glycol [] methyl trimethicone [] hdi/trimethylol hexyllactone crosspolymer [] lauryl peg-9 polydimethylsiloxyethyl dimethicone [] peg-100 stearate [] butyloctyl salicylate [] jojoba esters [] glyceryl stearate [] barosma betulina leaf oil*, citrus paradisi (grapefruit) peel oil*, eucalyptus globulus (eucalyptus) leaf oil*, abies sibirica (pine) oil*, prunus amygdalus amara (bitter almond) kernel oil*, mentha arvensis (field mint) leaf oil*, rosa damascena (rose) oil*, limonene [] panax ginseng (ginseng) root extract [] cordyceps sinensis extract [] garcinia mangostana peel extract [] castanea sativa (chestnut) seed extract [] hordeum vulgare (barley) extract\extrait d'orge [] triticum vulgare (wheat) germ extract [] laminaria saccharina extract [] mangifera indica (mango) seed butter [] butyrospermum parkii (shea butter) [] caffeine [] cholesterol [] potassium cetyl phosphate [] glyceryl polymethacrylate [] cetyl alcohol [] isopropyl myristate [] trehalose [] ethylhexylglycerin [] linoleic acid [] squalane [] polymethyl methacrylate [] dehydroxanthan gum [] ascorbyl tocopheryl maleate [] sodium hyaluronate [] caprylyl glycol [] ammonium acryloyldimethyltaurate/vp copolymer [] citric acid [] stearic acid [] silica [] sodium dehydroacetate [] phenoxyethanol [] mica [] iron oxides (ci 77491, ci 77492, ci 77499) [] titanium dioxide (ci 77891)

WARNINGS

warning: keep out of eyes. stop use if irritation occurs. keep out of reach of children.

PACKAGE LABEL

principal display panel:

origins

Vitazing SPF 15

Energy Boosting Moisturizer

with Mangosteen

1.7 fl oz./oz liq/50 ml

origins natural resources inc

new york, ny 10022